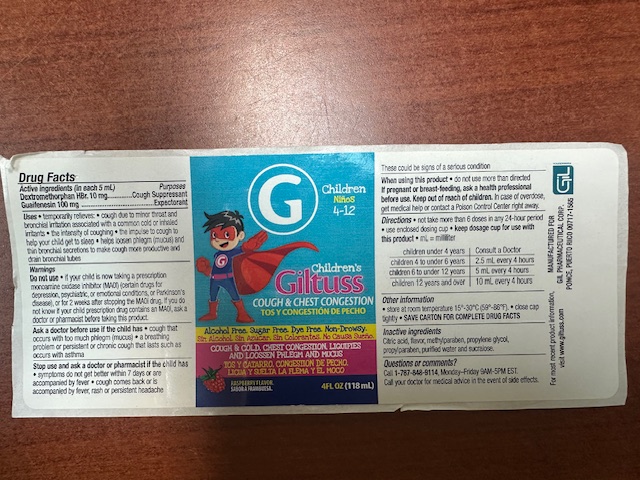 DRUG LABEL: Giltuss Childrens Cough and Chest Congestion
NDC: 65852-019 | Form: SOLUTION
Manufacturer: Dextrum Laboratories, Inc
Category: otc | Type: HUMAN OTC DRUG LABEL
Date: 20251006

ACTIVE INGREDIENTS: GUAIFENESIN 100 mg/5 mL; DEXTROMETHORPHAN HYDROBROMIDE 10 mg/5 mL
INACTIVE INGREDIENTS: METHYLPARABEN; CITRIC ACID; PROPYLPARABEN; SUCRALOSE; WATER; PROPYLENE GLYCOL

Indication and usage section

Not take more than 6 doses in any 24 hours period.

Use enclosed dosing cup. keep dosage cup for use with this product

ML=Milliliters

Children under 4 years, consult a doctor

Children 4 to under 6 years, 2.5 ml every 4 hours

Children 6 to under 12 years, 5 ml every 4 hours

Children 12 years and over, 10 ml every 4 hours

Active ingredient section

(in each 5 ml)

Dextromethorphan HBr 10 mg

Guaifenesin 100 mg

Active ingredient section

Inactive ingredient

Citric acid, flavor, methylparaben, propylene glycol, propylparaben, purified water and sucralose.

Purpose section

Cough suppressant

Expectorant

Warnings

Do not use if you child is now taking a prescription monoamine oxidase inhibitor(MAOI) (certain drugs for depression, psychiatric or emotional condition, or Parkinson's disease), or for 2 weeks after stopping the MAOI drug. If you do not know if your child prescription drug contains an MAOI ask a doctor or pharmacist before taking this product.

Keep out of reach of childrens section

In case of a overdose, get medical help or contacta Poison Control Center right away

Question section

Call 1-787-848-9114 Monday-Friday 9AM-5PM EST.

Call your doctor for medical advice in the event of side effects.

Ask a doctor section

Ask a doctor before use if the child has

cough that occurs with much phlegm(mucus)

a breathing problem or persistent or chronic cough that lasts such as occurs with asthma.

stop use section

Stop use ans ask doctor of pharmacist if the child has symptoms do not get better within 7 days or are accompanied by fever, cough comes back or is accompanied by fever rash or persistent headache.

Dosage and Administratiion section

Not take more than 6 doses in any 24 hours period.

Use enclosed dosing cup. keep dosage cup for use with this product

ML=Milliliters

Children under 4 years, consult a doctor

Children 4 to under 6 years, 2.5 ml every 4 hours

Children 6 to under 12 years, 5 ml every 4 hours

Children 12 years and over, 10 ml every 4 hours

Package Label. Principal Display Panel

G Children, ninos 4-12

Children's

Giltuss

Cough & Chest Congestion

Tos y Congestion de Pecho

Alcohol Free. Sugar Free. Dye Free. Non-Drowsy

Sin Alcohol. Sin Azucar. Sin Colorantes. No causa sueno.

COUGH & COLD, CHEST CONGESTION, LIQUIFIES

AND LOOSSEN PHLEGM AND MUCUS

TOS Y CATARRO, CONGESTION DE PECHO,

LIQUA Y SUELTA LA FLEMA Y EL MOCO

RASBERRY FLAVOIR.

SABOR A FRAMBUESA. 4 FL OZ (118 ml)